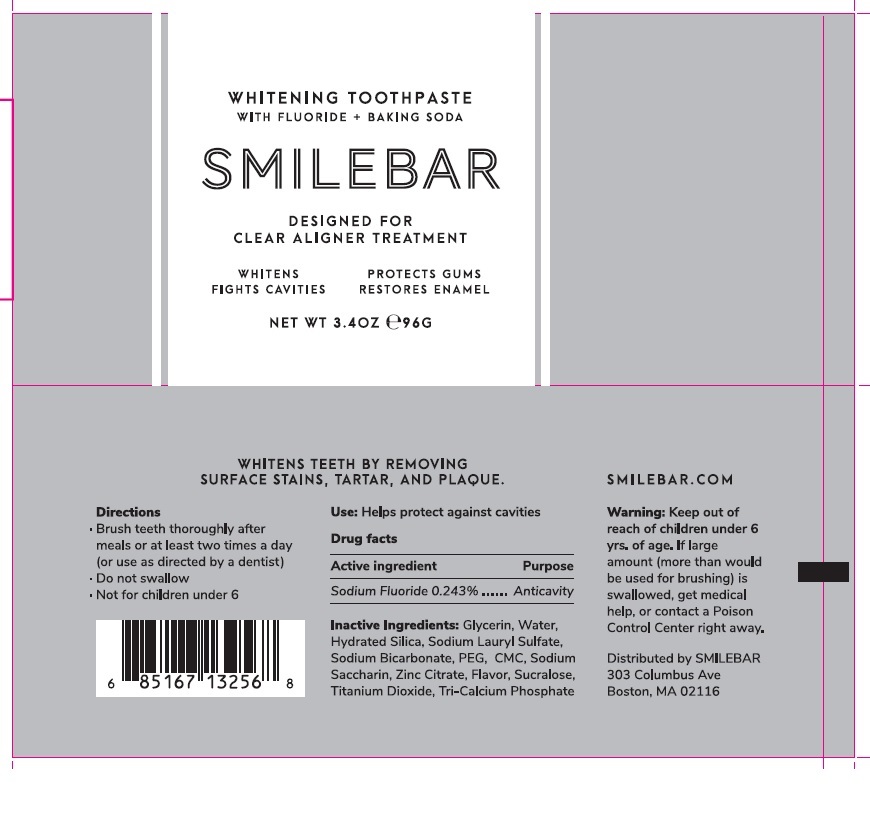 DRUG LABEL: SMILEBAR Whitening
NDC: 73449-001 | Form: PASTE, DENTIFRICE
Manufacturer: Smilebar
Category: otc | Type: HUMAN OTC DRUG LABEL
Date: 20201208

ACTIVE INGREDIENTS: SODIUM FLUORIDE 2.43 mg/1 g
INACTIVE INGREDIENTS: GLYCERIN; WATER; HYDRATED SILICA; SODIUM LAURYL SULFATE; SODIUM BICARBONATE; POLYETHYLENE GLYCOL 8000; CARBOXYMETHYLCELLULOSE; SACCHARIN SODIUM; ZINC CITRATE; SUCRALOSE; TITANIUM DIOXIDE; TRICALCIUM PHOSPHATE

SMILEBAR WHITENING TOOTHPASTE WITH FLUORIDE + BAKING SODA

Drug facts

Active ingredient

Sodium Fluoride 0.243%

Purpose

Anticavity

Uses

Helps protect against cavities

WARNINGS

Warnings: Keep out of reach of children under 6 yrs. of age.

If large amount (more than would be used for brushing) is swallowed, get medical help, or contact a Poison Control Center right away.

Directions

- Brush teeth thoroughly after

meals or at least two times a day

(or use as directed by a dentist)

- Do not swallow

- Not for children undre 6

Inactive ingredients: Glycerin, Water,

Hydrated Silica, Sodium Lauryl Sulfate,

Sodium Bicarbonate, PEG, CMC, Sodium

Saccharin, Zinc Citrate, Flavor, Sucralose,

Titanium Dioxide, Tri-calcium Phosphate

Package Labeling

WHITENING TOOTHPASTE

WITH FLUORIDE + BAKING SODA

DESIGNED FOR CLEAR ALIGNER TREATMENT

WHITENS PROTECTS GUMS

FIGHTS CAVITIES RESTORES ENAMEL

NET WT 3.4 OZ e96 G

WHITENS TEETH BY REMOVING

SURFACE STAINS, TARTER, AND PLAQUE SMILEBAR.COM

Distributed by SMILEBAR

303 Columbus Ave

Boston, MA 02116

res